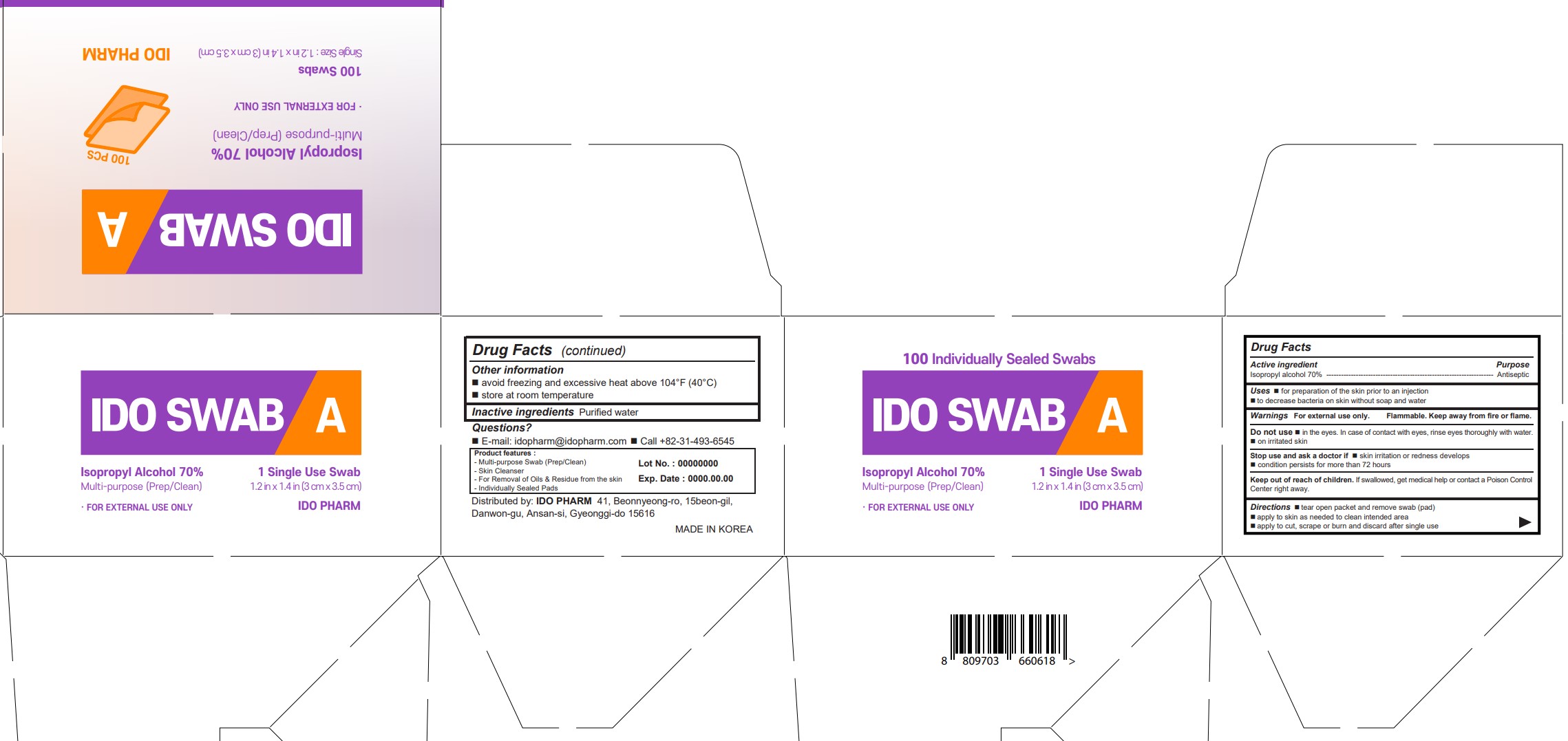 DRUG LABEL: IDO SWABA
NDC: 77039-025 | Form: LIQUID
Manufacturer: IDO PHARM
Category: otc | Type: HUMAN OTC DRUG LABEL
Date: 20230924

ACTIVE INGREDIENTS: ISOPROPYL ALCOHOL 70 mL/100 mL
INACTIVE INGREDIENTS: WATER

ACTIVE INGREDIENT

Isopropyl alcohol

INACTIVE INGREDIENT

water

PURPOSE

for preparation of the skin prior to an injection

to decrease bacteria on skin without soap and water

Keep out of reach of children

INDICATIONS AND USAGE

Directions  tear open packet and remove swab (pad)  apply to skin as needed to clean intended area  apply to cut, scrape or burn and discard after single use

Do not use  in the eyes. In case of contact with eyes, rinse eyes thoroughly with water.  on irritated skin

Stop use and ask a doctor if  skin irritation or redness develops  condition persists for more than 72 hours

Keep out of reach of children. If swallowed, get medical help or contact a Poison Control Center right away.

DOSAGE AND ADMINISTRATION

For external use only